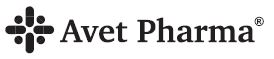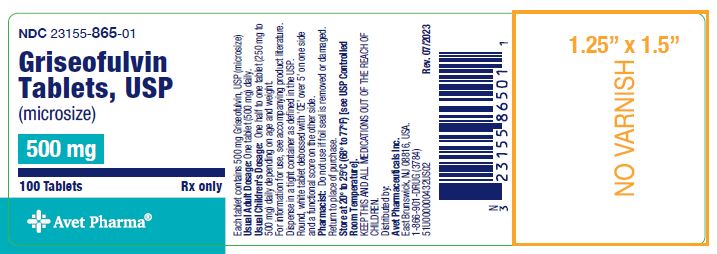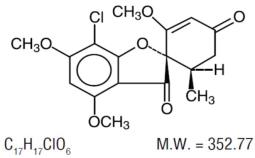 DRUG LABEL: GRISEOFULVIN MICROSIZE
NDC: 23155-865 | Form: TABLET
Manufacturer: Heritage Pharmaceuticals Inc d/b/a Avet Pharmaceuticals Inc
Category: prescription | Type: HUMAN PRESCRIPTION DRUG LABEL
Date: 20251104

ACTIVE INGREDIENTS: GRISEOFULVIN 500 mg/1 1
INACTIVE INGREDIENTS: MAGNESIUM STEARATE; POLOXAMER 188; STARCH, POTATO; SILICON DIOXIDE

GRISEOFULVIN TABLETS, USP (MICROSIZE)
500 MG
Rx ONLY

DESCRIPTION

Griseofulvin tablets, USP (microsize) contain griseofulvin microsize for oral administration. The active ingredient, griseofulvin, is a fungistatic antibiotic, derived from a species of Penicillium. The chemical name of griseofulvin is 7-chloro-2’,4,6-trimethoxy-6’β-methylspiro[benzofuran-2(3H),1’-[2]cyclohexane]-3-4’-dione. Its structural formula is:

Griseofulvin, USP occurs as a white to creamy white, odorless powder which is very slightly soluble in water, soluble in acetone, dimethylformamide, and chloroform and sparingly soluble in alcohol.

Each griseofulvin tablet contains 500 mg of microsized griseofulvin.

The inactive ingredients for griseofulvin tablets 500 mg, include: magnesium stearate, poloxamer 188, potato starch, and colloidal silicon dioxide.

CLINICAL PHARMACOLOGY

Griseofulvin absorption from the gastrointestinal tract varies considerably among individuals, mainly because of insolubility of the drug in aqueous media of the upper GI tract. Drug absorption has been estimated to range between 27 and 72%. After an oral dose, griseofulvin is primarily absorbed from the duodenum with some absorption occurring from the jejunum and ileum. The peak serum level in fasting adults given 0.5 g of griseofulvin microsize occurs at about four hours and ranges between 0.5 to 2 mcg/mL. The serum level may be increased by giving the drug with a meal with a high fat content. In one study in pediatric patients 19 months to 11 years of age, 10 mg/kg of griseofulvin microsize given with milk resulted in mean peak serum concentrations approximately four-fold greater than the same griseofulvin dose given alone (1.29 mcg/mL versus 0.34 mcg/mL, respectively). Also, the area under the curve value was ten-fold larger when 10 mg/kg griseofulvin and milk were administered simultaneously as compared to the same dosage given to fasting patients. In addition, griseofulvin administered with milk resulted in more consistently detected serum levels across subjects.

Following oral administration, griseofulvin is deposited in the keratin precursor cells and has a greater affinity for diseased tissue. The drug is tightly bound to the new keratin which becomes highly resistant to fungal invasions. When the drug is discontinued, griseofulvin concentrations in the skin decline less rapidly than those in plasma. Griseofulvin is metabolized by the liver to 6-desmethylgriseofulvin and its glucuronide conjugate.

Griseofulvin has a variable elimination half-life in plasma (9 to 24 hours). Approximately 30% of a single oral dose of griseofulvin is excreted in the urine within 24 hours and about 50% of the dose is excreted in the urine within 5 days, mostly in the form of metabolites. Unchanged griseofulvin in the urine accounts for less than 1% of the administered dose. In addition, approximately one-third of a single dose of griseofulvin is excreted in feces within 5 days. Griseofulvin is also excreted in perspiration.

Microbiology
Mechanism of Action

The mechanism of griseofulvin consists of binding microtubular proteins, which are required for mitosis.

Activity In Vivo
Griseofulvin may be active against most strains of the following dermatophytes as described in the INDICATIONS AND USAGE section:

Epidermophyton floccosum, Microsporum audouinii, Microsporum canis, Microsporum gypseum, Trichophyton crateriformis, Trichophyton gallinae, Trichophyton interdigitalis, Trichophyton megnini, Trichophyton mentagrophytes, Trichophyton rubrum, Trichophyton sulphureum, Trichophyton schoenleini, Trichophyton tonsurans and Trichophyton verrucosum.

It has no effect on bacteria or on other genera of fungi.

Activity In Vitro
In vitro, griseofulvin has been shown to have activity against many dermatophytes, but the clinical significance is unknown.

Drug Resistance
Although there have been reports of dermatophyte resistance to griseofulvin, the clinical significance is unknown.

INDICASTIONS AND USAGE

Griseofulvin tablets, USP are indicated for the treatment of dermatophyte infections of the skin not adequately treated by topical therapy, hair and nails, namely:

Tinea corporis

Tinea pedis

Tinea cruris

Tinea barbae

Tinea capitis

Tinea unguium when caused by one or more of the following species of fungi:

Epidermophyton floccosum

Microsporum audouinii

Microsporum canis

Microsporum gypseum

Trichophyton crateriform

Trichophyton gallinae

Trichophyton interdigitalis

Trichophyton megnini

Trichophyton mentagrophytes

Trichophyton rubrum

Trichophyton schoenleini

Trichophyton sulphureum

Trichophyton tonsurans

Trichophyton verrucosum

Note: Prior to therapy, a dermatophyte should be identified as responsible for the infection. Prior to initiating treatment, appropriate specimens for laboratory testing (KOH preparation, fungal culture, or nail biopsy) should be obtained to confirm the diagnosis. Griseofulvin tablets, USP are not effective in the following:

Bacterial infections

Candidiasis (Moniliasis)

Histoplasmosis

Actinomycosis

Sporotrichosis

Chromoblastomycosis

Coccidioidomycosis

North American Blastomycosis

Cryptococcosis (Torulosis)

Tinea versicolor

Nocardiosis

The use of this drug is not justified in minor or trivial dermatophyte infections which will respond to topical agents alone.

CONTRAINDICATIONS

Griseofulvin is contraindicated in patients with porphyria or hepatocellular failure, and in individuals with a history of hypersensitivity to griseofulvin.

Griseofulvin may cause fetal harm when administered to a pregnant woman. Two published cases of conjoined twins have been reported in patients taking griseofulvin during the first trimester of pregnancy, therefore, griseofulvin is contraindicated in women who are or may become pregnant during treatment. Women taking estrogen-containing oral contraceptives may be at increased risk of becoming pregnant while on griseofulvin (see also PRECAUTIONS, Drug Interactions). If this drug is used during pregnancy, or if the patient becomes pregnant while taking this drug, the patient should be apprised of the potential hazard to the fetus. Although no direct causal relationship has been established, spontaneous abortion has been reported rarely coincident with the use of griseofulvin.

Note: The Maximum Recommend Human Dose (MRHD) was set at 500 mg/day for the multiple of human exposure calculations performed in this label. If higher doses than 500 mg/day were used clinically, then the multiple of human exposure would be correspondingly reduced for that dose. For example, if a 1,000 mg/day dose was administered to an individual, then the multiple of human exposure would be reduced by a factor of 2.

Griseofulvin has been shown to be embryotoxic and teratogenic in pregnant rats when given at a daily oral dose of 250 mg/kg/day [4X the Maximum Recommended Human Dose (MRHD) based on Body Surface Area (BSA)]. Griseofulvin also has been shown to be embryotoxic and teratogenic in pregnant cats treated weekly with griseofulvin at doses of 500 to 1,000 mg/week. There are reports of teratogenicity in a Golden Retriever when doses of 750 mg/day [1.2X the MRHD based on BSA] were administered for four weeks prior to and throughout the pregnancy, and in a study in which beagles were administered 35 mg/kg/day [1.9X the MRHD based on BSA] for intervals from one week up to the entire gestation period. Teratogenicity was also seen in mice when griseofulvin was administered in doses equivalent to 5g/kg/day [40X the MRHD based on BSA] for 2 consecutive days at various stages of the pregnancy.

WARNINGS

Prophylactic Usage

Safety and efficacy of griseofulvin for prophylaxis of fungal infections have not been established.

Serious Skin Reactions

Severe skin reactions (e.g. Stevens-Johnson syndrome, toxic epidermal necrolysis) and erythema multiforme have been reported with griseofulvin use. These reactions may be serious and may result in hospitalization or death. If severe skin reactions occur, griseofulvin should be discontinued (see ADVERSE REACTIONS section).

Hepatotoxicity

Elevations in AST, ALT, bilirubin, and jaundice have been reported with griseofulvin use. These reactions may be serious and may result in hospitalization or death. Patients should be monitored for hepatic adverse events and discontinuation of griseofulvin considered if warranted (see ADVERSE REACTIONS section).

PRECAUTIONS

General

Patients on prolonged therapy with any potent medication should be under close observation. Periodic monitoring of organ system function, including renal, hepatic and hematopoietic, should be done.
Since griseofulvin is derived from species of penicillin, the possibility of cross sensitivity with penicillin exists; however, known penicillin-sensitive patients have been treated without difficulty.
Lupus erythematosus, lupus-like syndromes or exacerbation of existing lupus erythematosus have been reported in patients receiving griseofulvin.

Since a photosensitivity reaction is occasionally associated with griseofulvin therapy, patients should be warned to avoid exposure to intense or prolonged natural or artificial sunlight.

Drug Interactions

Griseofulvin has been reported in the literature to interfere with the metabolism of various compounds. Whether this is due to a P-450 mediated enzyme induction effects on sulfurtransferase and/or glucotransferase activity, or some other mechanism is unknown.
Griseofulvin decreases the activity of warfarin-type anticoagulants, so that patients receiving these drugs concomitantly may require dosage adjustment of the anticoagulant during and after griseofulvin therapy.

Griseofulvin may enhance the hepatic metabolism of estrogens, including the estrogen component of oral contraceptives, thereby reducing the effectiveness of contraception and causing menstrual irregularities. Therefore, an alternate or second form of birth control may be indicated during periods of concurrent use (see also CONTRAINDICATIONS).

Cyclosporine levels may be reduced when administered concomitantly with griseofulvin, resulting in a decrease in the pharmacologic effects of cyclosporine.

Serum salicylate concentrations may be decreased when griseofulvin is given concomitantly with salicylates.

Barbiturates usually depress griseofulvin activity by decreasing plasma levels and concomitant administration may require a dosage adjustment of the antifungal agent.

Nausea, vomiting, flushing, tachycardia, and severe hypotension have been reported following alcohol ingestion during griseofulvin therapy.

Carcinogenesis , Mutagenesis , Impairment of Fertility

In subacute toxicity studies, orally administered griseofulvin produced hepatocellular necrosis in mice, but this has not been seen in other species. Chronic feeding of griseofulvin, at levels ranging from 0.5 to 2.5% of the diet, resulted in the development of liver tumors in several strains of mice, particularly in males. Smaller particle sizes resulted in an enhanced effect. Lower oral-dosage levels have not been tested.

Subcutaneous administration of relatively small doses of griseofulvin once a week during the first three weeks of life has also been reported to induce hepatomata in mice. Thyroid tumors, mostly adenomas but some carcinomas, have been reported in male rats receiving griseofulvin at levels of 2%, 1%, and 0.2% of the diet, and in female rats receiving the two higher dose levels. Studies in other animal species were inadequate assessments of tumorigenicity.

Disturbances in porphyrin metabolism have been reported in griseofulvin-treated laboratory animals. Griseofulvin has been reported to have a colchicine-like effect on mitosis and was co-carcinogenic with methylcholanthrene in cutaneous tumor induction in laboratory animals. Griseofulvin interferes with chromosomal distribution during cell division, causing aneuploidy in plant and mammalian cells. These effects have been demonstrated in vitro at concentrations that may be achieved in the serum with the recommended therapeutic dosage.

Suppression of spermatogenesis has been reported to occur in rats and sperm abnormalities have been observed in griseofulvin treated mice, but these were not detected in man. Male patients should wait at least six months after completing griseofulvin therapy before fathering a child.

Pregnancy

Teratogenic Effects

Pregnancy Category X

See CONTRAINDICATIONS and PRECAUTIONS, Drug Interactions.

Nursing Mothers

It is not known if griseofulvin is excreted in human milk. Because many drugs are excreted in human milk and because of the potential for tumorigenicity shown for griseofulvin in animal studies (see PRECAUTIONS, Carcinogenesis, Mutagenesis, Impairment of Fertility), a decision should be made whether to discontinue nursing or to discontinue the drug, taking into account the importance of the drug to the mother.

Pediatric Use

Safety and effectiveness in pediatric patients 2 years of age and younger have not been established.

Safety in pediatric patients older than 2 years of age at dosages greater than 10 mg/kg daily has not been established.

ADVERSE REACTIONS

There have been post-marketing reports of severe skin and hepatic adverse events associated with griseofulvin use (see WARNINGS section).

When adverse reactions occur, they are most commonly of the hypersensitivity type, such as skin rashes, urticaria, and rarely, angioneurotic edema, and erythema multiforme. These may necessitate withdrawal of therapy and appropriate countermeasures.

Peripheral neuropathy and paresthesias of the hands and feet have been reported and may be related to treatment duration. Most patients treated with griseofulvin for less than six months experienced improvement or resolution of their neuropathy upon withdrawal of the griseofulvin. Other side effects reported occasionally are oral thrush, nausea, vomiting, epigastric distress, diarrhea, headache, fatigue, dizziness, insomnia, mental confusion and impairment of performance of routine activities.

Proteinuria, nephrosis (sometimes associated with existing systemic lupus erythematosus), leukopenia, coagulopathy, hepatitis, elevated liver enzymes, hyperbilirubinemia, and GI bleeding have been reported rarely. Administration of the drug should be discontinued if granulocytopenia occurs.

To report SUSPECTED ADVERSE REACTIONS, contact Avet Pharmaceuticals Inc., at 1-866-901-DRUG (3784) or FDA at 1-800-FDA-1088 or www.fda.gov/medwatch.

OVERDOSAGE

There is limited experience on overdose with griseofulvin. In case of overdosage, discontinue medication, treat symptomatically and institute supportive measures as required.

DOSAGE AND ADMINISTRATION

Accurate diagnosis of the infecting organism is essential. Identification should be made either by direct microscopic examination of a mounting of infected tissue in a solution of potassium hydroxide or by culture on an appropriate medium.

Medication must be continued until the infecting organism is completely eradicated as indicated by appropriate clinical or laboratory examination. Representative treatment periods are tinea capitis, 4 to 6 weeks; tinea corporis, 2 to 4 weeks; tinea pedis, 4 to 8 weeks; tinea unguium – depending on rate of growth – fingernails, at least 4 months; toenails, at least 6 months.

General measures in regard to hygiene should be observed to control sources of infection or reinfection. Concomitant use of appropriate topical agents is usually required, particularly in treatment of tinea pedis. In some forms of tinea pedis, yeasts and bacteria may be involved as well as dermatophytes. Griseofulvin tablets, USP will not eradicate hese associated bacterial or yeast infections.

ADULTS: 0.5 g daily (125 mg q.i.d., 250 mg b.i.d., or 500 mg/day). Patients with less severe or 300 extensive infections may require less, whereas those with widespread lesions may require a starting dose of 0.75 g to 1 g/day. This may be reduced gradually to 0.5 g or less after a response has been noted. In all cases, the dosage should be individualized.

PEDIATRIC PATIENTS (older than 2 years): A dosage of 10 mg/kg daily is usually adequate (pediatric patients from 30 to 50 lb, 125 mg to 250 mg daily; pediatric patients over 50 lb, 250 mg to 500 mg daily, in divided doses). Dosage should be individualized, as with adults. Clinical relapse will occur if the medication is not continued until the infecting organism is eradicated.

Safety is not established at higher doses than recommended.

HOW SUPPLIED

Griseofulvin Tablets, USP (microsize) 500 mg: are supplied as white to off white, round, scored tablets, debossed with ‘CE’ over ‘5’ on one side and a functional score on the other side.

They are available as follows:

Bottles of 100 tablets NDC 23155-865-01

Store at 20° to 25°C (68° to 77°F). [see USP Controlled Room Temperature].

Manufactured by: Chartwell Pharmaceuticals, LLC.
Congers, NY 10920

Distributed by:

Avet Pharmaceuticals Inc.
East Brunswick, NJ 08816
1.866.901.DRUG (3784)

Made in USA

51U000000434US01

Rev. 06/2023

PACKAGE LABEL

NDC 23155-865-01

Griseofulvin Tablets, USP

(microsize)

500 mg

100 Tablets

Rx Only